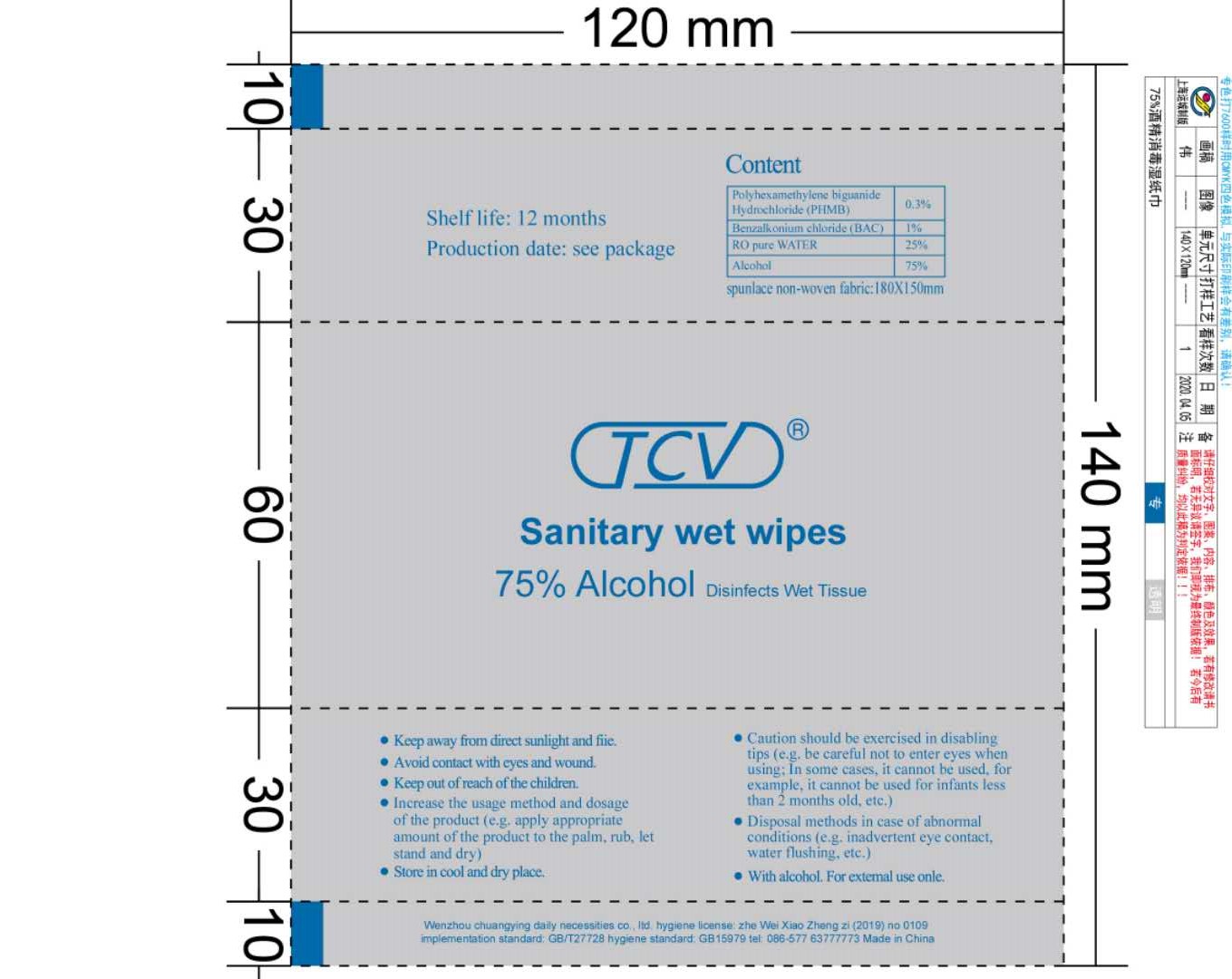 DRUG LABEL: Sanitary wet wipes
NDC: 78314-101 | Form: CLOTH
Manufacturer: Wenzhou Chuangying Daily Necessities Co., Ltd
Category: otc | Type: HUMAN OTC DRUG LABEL
Date: 20200531

ACTIVE INGREDIENTS: ALCOHOL 1.75 mL/1 1
INACTIVE INGREDIENTS: BENZALKONIUM CHLORIDE; WATER; POLIHEXANIDE HYDROCHLORIDE

Chuangying, 75% Alcohol Wipes

Active ingredient

Ethyl Alcohol 75% v/v. Purpose: Antiseptic

Purpose

Antiseptic.

When using

Avoid contact with eyes and wound.

Be careful not to enter eyes.

If it gets into eyes accidentally, please wash it with plenty of water.

Do not use

It cannot be used for infants less than 2 months old.

Stop use

Stop use if irritation and redness develop. If condition continues, consult your health care practitioner.

Keep out of reach of children

Keep out of reach of the children.

Indications & usage

This product is suitable for wiping hands, face, skin, etc.

Directions

Apply appropriate amount of the product to the palm, rub, let stand and dry.

Warnings

For external use only.

Flammable, please stay away from fire or heat.

Other information

Store in cool and dry place.

Keep away from direct sunlight and fire.

Inactive ingredient

Polyhexamethylene biguanide Hydrochloride (PHMB), Benzalkonium chloride (BAC), Water.